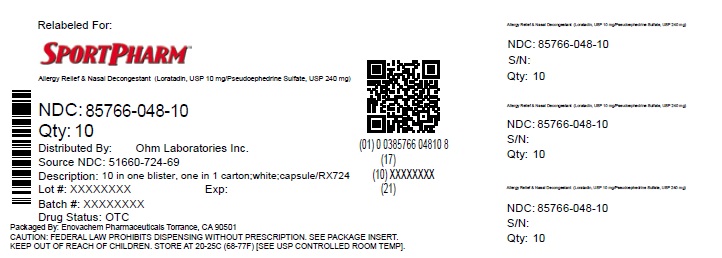 DRUG LABEL: Loratadine and Pseudoephedrine
NDC: 85766-048 | Form: TABLET, EXTENDED RELEASE
Manufacturer: Sportpharm LLC
Category: otc | Type: HUMAN OTC DRUG LABEL
Date: 20260206

ACTIVE INGREDIENTS: LORATADINE 10 mg/1 1; PSEUDOEPHEDRINE SULFATE 240 mg/1 1
INACTIVE INGREDIENTS: CALCIUM CARBONATE; SILICON DIOXIDE; HYDROXYPROPYL CELLULOSE (1600000 WAMW); HYPROMELLOSE, UNSPECIFIED; LACTOSE MONOHYDRATE; MAGNESIUM STEARATE; MICROCRYSTALLINE CELLULOSE; POVIDONE, UNSPECIFIED; STARCH, CORN; PROPYLENE GLYCOL; SHELLAC; SODIUM ALGINATE; SODIUM CITRATE, UNSPECIFIED FORM; TALC; TITANIUM DIOXIDE; FERROSOFERRIC OXIDE; POLYETHYLENE GLYCOL, UNSPECIFIED

DRUG FACTS

ACTIVE INGREDIENTS (IN EACH TABLET)

Loratadine, USP 10 mg

Pseudoephedrine sulfate, USP 240 mg

PURPOSE

Antihistamine

Nasal decongestant

USES

- temporarily relieves these symptoms due to hay fever or other upper respiratory allergies:
  - sneezing
  - itchy, watery eyes
  - runny nose
  - itching of the nose or throat
- reduces swelling of nasal passages
- temporarily relieves sinus congestion and pressure
- temporarily relieves nasal congestion due to the common cold, hay fever or other upper respiratory allergies
- temporarily restores freer breathing through the nose

WARNINGS

Do not use

- if you have ever had an allergic reaction to this product or any of its ingredients
- if you are now taking a prescription monoamine oxidase inhibitor (MAOI) (certain drugs for depression, psychiatric, or emotional conditions, or Parkinson's disease), or for 2 weeks after stopping the MAOI drug. If you do not know if your prescription drug contains an MAOI, ask a doctor or pharmacist before taking this product.

Ask a doctor before use if you have

- heart disease
- thyroid disease
- high blood pressure
- diabetes
- trouble urinating due to an enlarged prostate gland
- liver or kidney disease. Your doctor should determine if you need a different dose.

When using this product do not take more than directed.

Taking more than directed may cause drowsiness.

Stop use and ask a doctor if

- an allergic reaction to this product occurs. Seek medical help right away.
- symptoms do not improve within 7 days or are accompanied by a fever.
- nervousness, dizziness or sleeplessness occurs

If pregnant or breast-feeding

Ask a health professional before use.

Keep out of reach of children.

In case of overdose, get medical help or contact a Poison Control Center right away (1-800-222-1222).

DIRECTIONS

- do not divide, crush, chew or dissolve the tablet
  adults and children 12 years and over | 1 tablet daily with a full glass of water; not more than 1 tablet in 24 hours
  children under 12 years of age | ask a doctor
  consumers with liver or kidney disease | ask a doctor

OTHER INFORMATION

- sodium: contains 10 mg/tablet
- calcium: contains 25 mg/tablet
- TAMPER EVIDENT: DO NOT USE IF BLISTER UNITS ARE TORN, BROKEN OR SHOW ANY SIGNS OF TAMPERING.
- store between 20° C to 25° C (68° F to 77° F)
- protect from light and store in a dry place

INACTIVE INGREDIENTS

Calcium carbonate, colloidal silicon dioxide, hydroxypropyl cellulose, hypromellose, iron oxide black, lactose monohydrate, magnesium stearate, microcrystalline cellulose, polyethylene glycol, povidone, pregelatinized starch, propylene glycol, shellac glaze, sodium alginate, sodium citrate, talc and titanium dioxide

QUESTIONS?

Call 1-800-406-7984